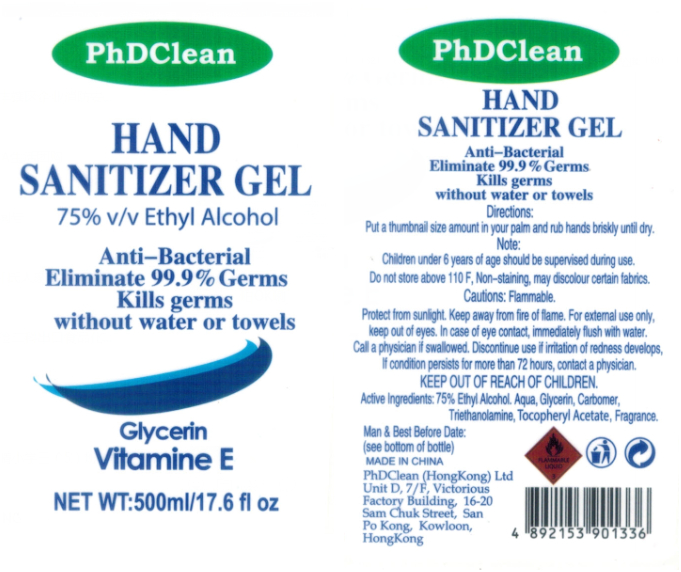 DRUG LABEL: PhDClean  Hand Sanitizer Gel
NDC: 52720-007 | Form: GEL
Manufacturer: ZHONGSHAN S. JANE BIOTECHNOLOGY CO., LTD.
Category: otc | Type: HUMAN OTC DRUG LABEL
Date: 20200706

ACTIVE INGREDIENTS: ALCOHOL 375 mL/500 mL
INACTIVE INGREDIENTS: .ALPHA.-TOCOPHEROL ACETATE; FRAGRANCE LAVENDER & CHIA F-153480; CARBOMER HOMOPOLYMER, UNSPECIFIED TYPE; WATER; TROLAMINE; GLYCERIN

DOSAGE AND ADMINISTRATION

Flammable. Keep away from fire or flame.

INACTIVE INGREDIENT

Aqua，Glycerin，Carbomer，Triethanolamine,Tocopheryl Acetate，Fragrance

INDICATIONS AND USAGE

Squeeze small amount in your palm and briskly rub hands together until dry.

ACTIVE INGREDIENT

Ethyl Alcohol

keep out of reach of children

PURPOSE

Disinfection
Sterilization
No Rinseing

WARNINGS

Flammable. Keep away from fire or flame.For external use only. Keep out of reach of children. Keep out of reach of eyes.